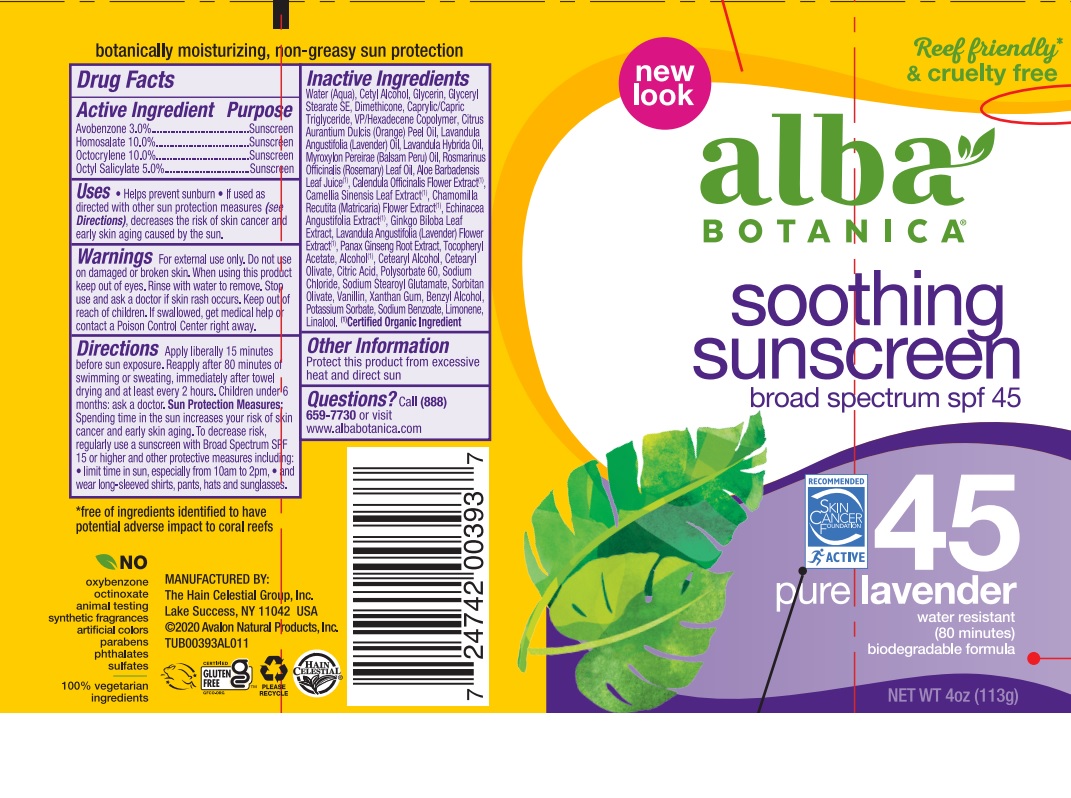 DRUG LABEL: Alba Botanica Pure Lavender Sunscreen SPF45
NDC: 61995-2093 | Form: LOTION
Manufacturer: The Hain Celestial Group, Inc.
Category: otc | Type: HUMAN OTC DRUG LABEL
Date: 20221202

ACTIVE INGREDIENTS: HOMOSALATE 10 g/100 g; OCTISALATE 5 g/100 g; OCTOCRYLENE 10 g/100 g; AVOBENZONE 3 g/100 g
INACTIVE INGREDIENTS: LAVENDER OIL; LAVANDULA ANGUSTIFOLIA FLOWER; ALCOHOL; BENZYL ALCOHOL; ALOE VERA LEAF; GLYCERIN; WATER; VINYLPYRROLIDONE/HEXADECENE COPOLYMER; SODIUM STEAROYL GLUTAMATE; .ALPHA.-TOCOPHEROL ACETATE; GLYCERYL STEARATE SE; POTASSIUM SORBATE; CETYL ALCOHOL; DIMETHICONE; GREEN TEA LEAF; CHAMOMILE; XANTHAN GUM; CETOSTEARYL ALCOHOL; POLYSORBATE 60; MEDIUM-CHAIN TRIGLYCERIDES; CALENDULA OFFICINALIS FLOWER; GINKGO; CETEARYL OLIVATE; SODIUM CHLORIDE; SORBITAN OLIVATE; SODIUM BENZOATE; ORANGE OIL; ASIAN GINSENG; CITRIC ACID MONOHYDRATE; LAVANDIN OIL; ROSEMARY OIL; BALSAM PERU OIL

Alba Botanica Pure Lavender Sunscreen SPF45

Active Ingredient

Avobenzone - 3.0%

Homosalate - 10.0%

Octocrylene - 10.0%

Ethylhexyl Salicylate - 5.0%

DOSAGE AND ADMINISTRATION

Apply liberally 15 minutes before sun exposure. Reapply after 80 minutes of swimming or sweating, immediately after towel drying and at least every 2 hours.

PURPOSE

Sunscreen

WARNINGS

For external use only. Do not use on damaged or broken skin. When using this product keep out of eyes. Rinse with water to remove. Stop use and ask a doctor if skin rash occurs.

Keep out of reach of children. If swallowed get medical help or contact Poison Center right away.

INACTIVE INGREDIENT

Water, Cetyl Alcohol, Glycerin, Glyceryl Stearate SE, Dimethicone, Caprylic/Capric Triglyceride, VP/Hexadecene Copolymer, Citrus Aurantium Dulcis (Orange) Peel Oil, Lavandula Angustifolia (Lavender) Oil, Lavandula Hybrida Oil, Myrohylon Pereairae (Balsam Pery) oil, Rosmarinus Officinalis (Rosemary) Leaf Oil, Aloe Barbadensis Leaf Juice(1), Calendula Officinalis Flower Extract (1), Camellia Sinensis Leaf Extract (1), Chamomilla Recutita (Matricaria) Flower Extract (1), Echinacea Angustifolia Extract (1), Ginkgo Biloba Leaf Extract, Lavandula Angustifolia (Lavender) Extract (1), Panax Ginseng Root Extract, Tocopheryl Acetate, Alcohol (1), Cetearyl Alcohol, Cetearyl Olivate, Citric Acid, Polysorbate 60, Sodium Chloride, Sodium Stearoyl Glutamate, Sorbitan Olivate, Vanillin, Xanthan Gum, Benzyl Alcohol, Potassium Sorbate, Sodium Benzoate, Limonene, Linalool.

(1) Certified Organic Ingredient

INDICATIONS AND USAGE

Helps prevents sunburns. If used as directed with other sun protection measures, decreases risk of skin cancer and early skin aging caused by sun exposure. Skin Protection Measures: Spending time in the sun increases your risk of skin cancer and early skin aging. To decrease risk, regularly use sunscreen with Broad Spectrum SPF 15 or higher and other protective measures including: limit time in sun, especially from10am to 2pm, and wear long sleeved shirts, pants, hats and sunglases.